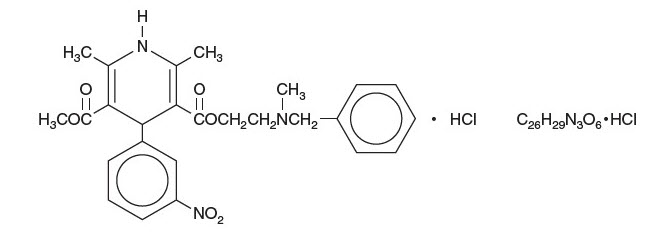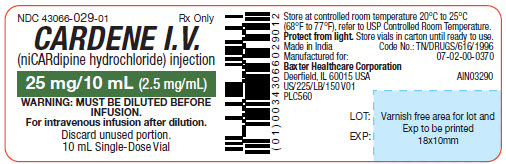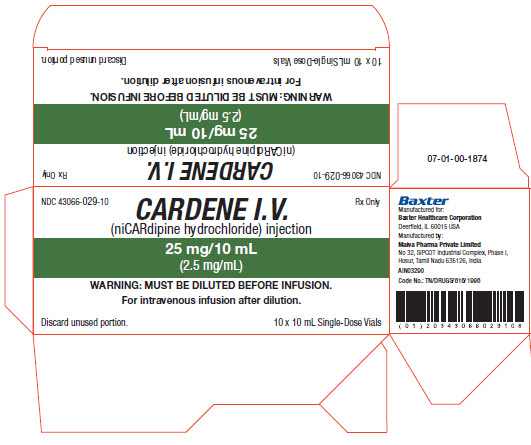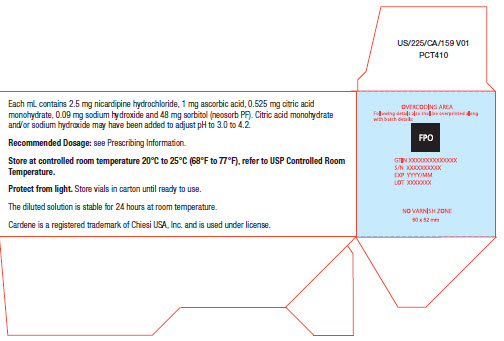 DRUG LABEL: CARDENE IV
NDC: 43066-029 | Form: INJECTION, SOLUTION
Manufacturer: Baxter Healthcare Corporation
Category: prescription | Type: HUMAN PRESCRIPTION DRUG LABEL
Date: 20251229

ACTIVE INGREDIENTS: NICARDIPINE HYDROCHLORIDE 2.5 mg/10 mL
INACTIVE INGREDIENTS: ASCORBIC ACID 1 mg/10 mL; CITRIC ACID MONOHYDRATE 0.525 mg/10 mL; SODIUM HYDROXIDE 0.09 mg/10 mL; SORBITOL 48 mg/10 mL

HIGHLIGHTS OF PRESCRIBING INFORMATION

These highlights do not include all the information needed to use CARDENE IV safely and effectively. See full prescribing information for CARDENE IV.
CARDENE IV (nicardipine hydrochloride) injection, for intravenous use
Initial U.S. Approval: 1988

1 INDICATIONS AND USAGE

- CARDENE I.V. is a calcium channel blocker indicated for the short-term treatment of hypertension when oral therapy is not feasible. (1.1)

2 DOSAGE AND ADMINISTRATION

- For Intravenous Use. (2.1)
- Single-dose vials must be diluted before use. (2.3)
- When substituting for oral nicardipine therapy, use the intravenous infusion rate from the table below (2.1):

Oral CARDENE Dose | Equivalent I.V. Infusion Rate; (0.1 mg/mL)
20 mg q8h | 0.5 mg/hr = 5 mL/hr
30 mg q8h | 1.2 mg/hr = 12 mL/hr
40 mg q8h | 2.2 mg/hr = 22 mL/hr

- In a patient not receiving oral nicardipine, initiate therapy at 50 mL/hr (5 mg/hr) 0.1 mg/mL solution. Increase the infusion rate by 25 mL/hr (2.5 mg/hr) every 5 minutes (for rapid titration) to 15 minutes (for gradual titration) up to a maximum of 150 mL/hr (15 mg/hr) until desired blood pressure reduction is achieved. (2.1)
- If unacceptable hypotension or tachycardia occurs, discontinue the infusion. When blood pressure and heart rate stabilize, restart the infusion at low doses such as 30 mL/hr to 50 mL/hr (3 mg/hr to 5 mg/hr). (2.2)

3 DOSAGE FORMS AND STRENGTHS

Injection: 25 mg/10 mL (2.5 mg/mL) nicardipine hydrochloride in a single-dose vial for intravenous infusion. (3)

4 CONTRAINDICATIONS

- Do not use in patients with advanced aortic stenosis (4.1).

5 WARNINGS AND PRECAUTIONS

- Closely monitor response in patients with angina, heart failure, impaired hepatic function, or renal impairment. (5.1, 5.2, 5.3, 5.4)
- To reduce the possibility of venous thrombosis, phlebitis, and vascular impairment, do not use small veins, such as those on the dorsum of the hand or wrist. Exercise extreme care to avoid intra-arterial administration or extravasation. (5.5)
- To minimize the risk of peripheral venous irritation, change the site of infusion of CARDENE I.V. every 12 hours. (5.5)

6 ADVERSE REACTIONS

Most common adverse reactions: are headache (15%), hypotension (6%), tachycardia (4%) and nausea/vomiting (5%). (6.1)

To report SUSPECTED ADVERSE REACTIONS, contact Baxter Healthcare Corporation at 1-866-888-2472 or FDA at 1-800-FDA-1088 or www.fda.gov/medwatch.

7 DRUG INTERACTIONS

- Cimetidine increases oral nicardipine plasma levels. (7.2)
- Oral or intravenous nicardipine may increase cyclosporine and tacrolimus plasma levels. Frequent monitoring of trough blood levels of cyclosporine and tacrolimus is recommended when co-administering CARDENE I.V. (7.3, 7.4)

8 USE IN SPECIFIC POPULATIONS

- Pregnancy: Based on animal data may cause fetal harm. (8.1)
- Nursing mothers: Minimally excreted into human milk. (8.3)
- Safety and efficacy in patients under the age of 18 have not been established. (8.4)

FULL PRESCRIBING INFORMATION

1 INDICATIONS AND USAGE

1.1 Hypertension

CARDENE I.V. (nicardipine hydrochloride) is indicated for the short-term treatment of hypertension when oral therapy is not feasible or not desirable. For prolonged control of blood pressure, transfer patients to oral medication as soon as their clinical condition permits [see Dosage and Administration (2.1)].

2 DOSAGE AND ADMINISTRATION

2.1 Recommended Dosing

CARDENE I.V. is intended for intravenous use. Vial must be diluted to 0.1 mg/mL before use [see Dosage and Administration (2.3)]. Titrate dose to achieve the desired blood pressure reduction. Individualize dosage depending on the blood pressure to be obtained and the response of the patient.

Dosage as a Substitute for Oral Nicardipine Therapy

The intravenous infusion rate required to produce an average plasma concentration equivalent to a given oral dose at steady state is shown in the following table:

Oral CARDENE Dose | Equivalent I.V. Infusion Rate; (0.1 mg/mL)
20 mg q8h | 0.5 mg/hr = 5 mL/hr
30 mg q8h | 1.2 mg/hr = 12 mL/hr
40 mg q8h | 2.2 mg/hr = 22 mL/hr

Dosage for Initiation of Therapy in a Patient Not Receiving Oral Nicardipine
Initiate therapy at 50 mL/hr (5 mg/hr). If desired blood pressure reduction is not achieved at this dose, the infusion rate may be increased by 25 mL/hr (2.5 mg/hr) every 5 minutes (for rapid titration) to 15 minutes (for gradual titration) up to a maximum of 150 mL/hr (15 mg/hr), until desired blood pressure reduction is achieved.

Following achievement of the blood pressure goal utilizing rapid titration, decrease the infusion rate to 30 mL/hr (3 mg/hr).

Drug Discontinuation and Transition to an Oral Antihypertensive Agent
Discontinuation of infusion is followed by a 50% offset of action in about 30 minutes. If treatment includes transfer to an oral antihypertensive agent other than oral nicardipine, initiate therapy upon discontinuation of CARDENE I.V.
If oral nicardipine is to be used, administer the first dose 1 hour prior to discontinuation of the infusion.

Special Populations
Titrate CARDENE I.V. slowly in patients with heart failure or impaired hepatic or renal function [see Warnings and Precautions (5.2, 5.3 and 5.4)]

2.2 Monitoring

The time course of blood pressure decrease is dependent on the initial rate of infusion and the frequency of dosage adjustment. With constant infusion, blood pressure begins to fall within minutes. It reaches about 50% of its ultimate decrease in about 45 minutes.

Monitor blood pressure and heart rate continually during infusion and avoid too rapid or excessive blood pressure drop during treatment. If there is concern of impending hypotension or tachycardia, the infusion should be discontinued. Then, when blood pressure has stabilized, infusion of CARDENE I.V. may be restarted at low doses such as 30 mL/hr to 50 mL/hr (3 mg/hr to 5 mg/hr) and adjusted to maintain desired blood pressure.

2.3 Instructions for Administration

Administer CARDENE I.V. by a central line or through a large peripheral vein. Change the infusion site every 12 hours if administered via peripheral vein [see Warnings and Precautions (5.5)].

Preparation for administration
Single-dose vial must be diluted before infusion.

Inspection
As with all parenteral drugs, CARDENE I.V. should be inspected visually for particulate matter and discoloration prior to administration, whenever solution and container permit. CARDENE I.V. is normally a clear, pale yellow to yellow color solution and essentially, free from visible particles.

Dilution
CARDENE I.V. is administered by slow continuous infusion at a CONCENTRATION OF 0.1 MG/ML. Each vial (25 mg) should be diluted with 240 mL of compatible intravenous fluid (see below), resulting in 250 mL of solution at a concentration of 0.1 mg/mL.

CARDENE I.V. has been found to be compatible and stable in glass or polyvinyl chloride containers for 24 hours at controlled room temperature with:

- Dextrose (5%) Injection, USP
- Dextrose (5%) and Sodium Chloride (0.45%) Injection, USP
- Dextrose (5%) and Sodium Chloride (0.9%) Injection, USP
- Dextrose (5%) with 40 mEq Potassium, USP
- Sodium Chloride (0.45%) Injection, USP
- Sodium Chloride (0.9%) Injection, USP

CARDENE I.V. is NOT compatible with Sodium Bicarbonate (5%) Injection, USP or Lactated Ringer’s Injection, USP.

The diluted solution is stable for 24 hours at room temperature.

3 DOSAGE FORMS AND STRENGTHS

Injection: Nicardipine hydrochloride is a clear, pale yellow to yellow color solution supplied as 25 mg/10 mL (2.5 mg/mL) in a single-dose vial for intravenous infusion.

4 CONTRAINDICATIONS

4.1 Advanced Aortic Stenosis

CARDENE I.V. is contraindicated in patients with advanced aortic stenosis because part of the effect of CARDENE I.V. is secondary to reduced afterload. Reduction of diastolic pressure in these patients may worsen rather than improve myocardial oxygen balance.

5 WARNINGS AND PRECAUTIONS

5.1 Exacerbation of Angina

Increases in frequency, duration, or severity of angina have been seen in chronic therapy with oral nicardipine. Induction or exacerbation of angina has been seen in less than 1% of coronary artery disease patients treated with CARDENE I.V. The mechanism of this effect has not been established.

5.2 Exacerbation of Heart Failure

Titrate slowly when using CARDENE I.V., particularly in combination with a beta-blocker, in patients with heart failure or significant left ventricular dysfunction because of possible negative inotropic effects.

5.3 Increased effect with Impaired Hepatic Function

Since nicardipine is metabolized in the liver, consider lower dosages and closely monitor responses in patients with impaired liver function or reduced hepatic blood flow.

5.4 Prolonged effect with Impaired Renal Function

When CARDENE I.V. was given to mild to moderate hypertensive patients with moderate renal impairment, a significantly lower systemic clearance and higher area under the curve (AUC) was observed. These results are consistent with those seen after oral administration of nicardipine. Titrate gradually in patients with renal impairment.

5.5 Local Irritation

To reduce the possibility of venous thrombosis, phlebitis, local irritation, swelling, extravasation, and the occurrence of vascular impairment, administer drug through large peripheral veins or central veins rather than arteries or small peripheral veins, such as those on the dorsum of the hand or wrist. To minimize the risk of peripheral venous irritation, change the site of the drug infusion every 12 hours.

6 ADVERSE REACTIONS

6.1 Clinical Trials Experience

Because clinical trials are conducted under widely varying conditions, adverse reaction rates observed in the clinical trials of a drug cannot be directly compared to rates in the clinical trials of another drug and may not reflect the rates observed in practice. The adverse reaction information from clinical trials does, however, provide a basis for identifying the adverse events that appear to be related to drug use and for approximating rates.

Two hundred forty-four patients participated in two multicenter, double-blind, placebo-controlled trials of CARDENE I.V. Adverse experiences were generally not serious and most were expected consequences of vasodilation. Adverse experiences occasionally required dosage adjustment. Therapy was discontinued in approximately 12% of patients, mainly due to hypotension, headache, and tachycardia.

The table below shows percentage of patients with adverse events where the rate is >3% more common on CARDENE I.V. than placebo.

Adverse Event | CARDENE I.V. (N=144) | Placebo (N=100)
Body as a Whole
Headache, n (%) | 21 (15) | 2 (2)
Cardiovascular
Hypotension, n (%) | 8 (6) | 1 (1)
Tachycardia, n (%) | 5 (4) | 0
Digestive
Nausea/vomiting, n (%) | 7 (5) | 1 (1)

Other adverse events have been reported in clinical trials or in the literature in association with the use of intravenously administered nicardipine:

Body as a Whole: fever, neck pain

Cardiovascular: angina pectoris, atrioventricular block, ST segment depression, inverted T wave, deep-vein thrombophlebitis

Digestive: dyspepsia

Hemic and Lymphatic: thrombocytopenia

Metabolic and Nutritional: hypophosphatemia, peripheral edema

Nervous: confusion, hypertonia

Respiratory: respiratory disorder

Special Senses: conjunctivitis, ear disorder, tinnitus

Urogenital: urinary frequency

Sinus node dysfunction and myocardial infarction, which may be due to disease progression, have been seen in patients on chronic therapy with orally administered nicardipine.

6.2 Postmarketing Experience

Because adverse reactions are reported voluntarily from a population of uncertain size, it is not always possible to estimate reliably their frequency or to establish a causal relationship to drug exposure. The following adverse reaction has been identified during post-approval use of CARDENE I.V.: decreased oxygen saturation (possible pulmonary shunting).

7 DRUG INTERACTIONS

7.1 Beta-Blockers

In most patients, CARDENE I.V. can safely be used concomitantly with beta blockers. However, titrate slowly when using CARDENE I.V. in combination with a beta-blocker in heart failure patients [see Warnings and Precautions (5.2)].

7.2 Cimetidine

Cimetidine has been shown to increase nicardipine plasma concentrations with oral nicardipine administration. Frequently monitor response in patients receiving both drugs. Data with other histamine-2 antagonists are not available.

7.3 Cyclosporine

Concomitant administration of oral or intravenous nicardipine and cyclosporine results in elevated plasma cyclosporine levels through nicardipine inhibition of hepatic microsomal enzymes, including CYP3A4. Closely monitor plasma concentrations of cyclosporine during CARDENE I.V. administration, and reduce the dose of cyclosporine accordingly.

7.4 Tacrolimus

Concomitant administration of intravenous nicardipine and tacrolimus may result in elevated plasma tacrolimus levels through nicardipine inhibition of hepatic microsomal enzymes, including CYP3A4. Closely monitor plasma concentrations of tacrolimus during CARDENE I.V. administration, and adjust the dose of tacrolimus accordingly.

7.5 In Vitro Interaction

The plasma protein binding of nicardipine was not altered when therapeutic concentrations of furosemide, propranolol, dipyridamole, warfarin, quinidine, or naproxen were added to human plasma in vitro.

8 USE IN SPECIFIC POPULATIONS

8.1 Pregnancy

There are no adequate and well-controlled studies of nicardipine use in pregnant women. However, limited human data in pregnant women with preeclampsia or pre-term labor are available. In animal studies, no embryotoxicity occurred in rats with oral doses 8 times the maximum recommended human dose (MRHD) based on body surface area (mg/m^2), but did occur in rabbits with oral doses at 24 times the maximum recommended human dose (MRHD) based on body surface area (mg/m^2). CARDENE I.V. should be used during pregnancy only if the potential benefit justifies the potential risk to the fetus.

Hypotension, reflex tachycardia, postpartum hemorrhage, tocolysis, headache, nausea, dizziness, and flushing have been reported in pregnant women who were treated with intravenous nicardipine for hypertension during pregnancy. Fetal safety results ranged from transient fetal heart rate decelerations to no adverse events. Neonatal safety data ranged from hypotension to no adverse events.

Adverse events in women treated with intravenous nicardipine during pre-term labor include pulmonary edema, dyspnea, hypoxia, hypotension, tachycardia, headache, and phlebitis at site of injection. Neonatal adverse events include acidosis (pH<7.25).

In embryofetal toxicity studies, nicardipine was administered intravenously to pregnant rats and rabbits during organogenesis at doses up to 0.14 times the MRHD based on body surface area (mg/m^2) (5 mg/kg/day) (rats) and 0.03 times the MRHD based on body surface area (mg/m^2) (0.5 mg/kg/day) (rabbits). No embryotoxicity or teratogenicity was seen at these doses. Embryotoxicity, but no teratogenicity was seen at 0.27 times the MRHD based on body surface area (mg/m^2) (10 mg/kg/day) in rats and at 0.05 times the MRHD based on body surface area (mg/m^2) (1 mg/kg/day) in rabbits.

In other animal studies, pregnant Japanese White rabbits received oral nicardipine during organogenesis, at doses 8 and 24 times the MRHD based on body surface area (mg/m^2) (50 and 150 mg/kg/day). Embryotoxicity occurred at the high dose along with signs of maternal toxicity (marked maternal weight gain suppression). New Zealand albino rabbits received oral nicardipine during organogenesis, at doses up to 16 times the MRHD based on body surface area (mg/m^2)(100 mg nicardipine/kg/day). While significant maternal mortality occurred, no adverse effects on the fetus were observed. Pregnant rats received oral nicardipine from day 6 through day 15 of gestation at doses up to 8 times the MRHD based on body surface area (mg/m^2) (100 mg/kg/day). There was no evidence of embryotoxicity or teratogenicity; however, dystocia, reduced birth weights, reduced neonatal survival, and reduced neonatal weight gain were noted.

8.3 Nursing Mothers

Nicardipine is minimally excreted into human milk. Among 18 infants exposed to nicardipine through breast milk in the postpartum period, calculated daily infant dose was less than 0.3 mcg and there were no adverse events observed. Consider the possibility of infant exposure when using nicardipine in nursing mothers.

In a study of 11 women who received oral nicardipine 4 to 14 days postpartum, 4 women received immediate-release nicardipine 40 to 80 mg daily, 6 received sustained-release nicardipine 100 to 150 mg daily, and one received intravenous nicardipine 120 mg daily. The peak milk concentration was 7.3 mcg/L (range 1.9-18.8), and the mean milk concentration was 4.4 mcg/L (range 1.3-13.8). Infants received an average of 0.073% of the weight-adjusted maternal oral dose and 0.14% of the weight-adjusted maternal intravenous dose. In another study of seven women who received intravenous nicardipine for an average of 1.9 days in the immediate postpartum period as therapy for preeclampsia, 34 milk samples were obtained at unspecified times and nicardipine was undetectable (<5 mcg/L) in 82% of the samples. Four women who received 1 to 6.5 mg/hour of nicardipine had 6 milk samples with detectable nicardipine levels (range 5.1 to 18.5 mcg/L). The highest concentration of 18.5 mcg/L was found in a woman who received 5.5 mg/hour of nicardipine. The estimated maximum dose in a breastfed infant was < 0.3 mcg daily or between 0.015 to 0.004% of the therapeutic dose in a 1 kg infant.

8.4 Pediatric Use

Safety and efficacy in patients under the age of 18 have not been established.

8.5 Geriatric Use

The steady-state pharmacokinetics of nicardipine are similar in elderly hypertensive patients (>65 years) and young healthy adults.

Clinical studies of nicardipine did not include sufficient numbers of subjects aged 65 and over to determine whether they respond differently from younger subjects. Other reported clinical experience has not identified differences in responses between the elderly and younger patients. In general, use low initial doses in elderly patients, reflecting the greater frequency of decreased hepatic, renal or cardiac function, and of concomitant disease or other drug therapy.

10 OVERDOSAGE

Several overdosages with orally administered nicardipine have been reported. One adult patient allegedly ingested 600 mg of immediate-release oral nicardipine, and another patient, 2160 mg of the sustained-release formulation of nicardipine. Symptoms included marked hypotension, bradycardia, palpitations, flushing, drowsiness, confusion and slurred speech. All symptoms resolved without sequelae. An overdosage occurred in a one year old child who ingested half of the powder in a 30 mg nicardipine standard capsule. The child remained asymptomatic.

Based on results obtained in laboratory animals, lethal overdose may cause systemic hypotension, bradycardia (following initial tachycardia) and progressive atrioventricular conduction block. Reversible hepatic function abnormalities and sporadic focal hepatic necrosis were noted in some animal species receiving very large doses of nicardipine.

For treatment of overdosage, implement standard measures including monitoring of cardiac and respiratory functions. Position the patient so as to avoid cerebral anoxia. Use vasopressors for patients exhibiting profound hypotension.

11 DESCRIPTION

CARDENE I.V. (nicardipine hydrochloride) is a calcium ion influx inhibitor (slow channel blocker or calcium channel blocker). CARDENE I.V. for intravenous administration contains 20 mg (0.1 mg/mL) of nicardipine hydrochloride per 200 mL in either dextrose or sodium chloride or 40 mg (0.2 mg/mL) of nicardipine hydrochloride per 200 mL in sodium chloride. Nicardipine hydrochloride is a dihydropyridine derivative with IUPAC (International Union of Pure and Applied Chemistry) chemical name (±)-2-(benzyl-methyl amino) ethyl methyl 1,4-dihydro-2,6-dimethyl-4-(m-nitrophenyl)-3,5-pyridinedicarboxylate monohydrochloride and has the following structure:

Nicardipine hydrochloride is a greenish-yellow, odorless, crystalline powder that melts at about 169ºC. It is freely soluble in chloroform, methanol, and glacial acetic acid, sparingly soluble in anhydrous ethanol, slightly soluble in n-butanol, water, 0.01 M potassium dihydrogen phosphate, acetone, and dioxane, very slightly soluble in ethyl acetate, and practically insoluble in benzene, ether, and hexane. It has a molecular weight of 515.99.

CARDENE I.V. is available as sterile, non-pyrogenic, a clear, pale yellow to yellow color solution, and essentially free from visible particles, in 10 mL single-dose vial for intravenous infusion after dilution.

Each mL contains 2.5 mg nicardipine hydrochloride, 1 mg ascorbic acid, 0.525 mg citric acid monohydrate, 0.09 mg sodium hydroxide and 48 mg sorbitol (neosorb PF). Citric acid monohydrate and/or sodium hydroxide may have been added to adjust pH to 3.0 to 4.2.

12 CLINICAL PHARMACOLOGY

12.1 Mechanism of Action

Nicardipine inhibits the transmembrane influx of calcium ions into cardiac muscle and smooth muscle without changing serum calcium concentrations. The contractile processes of cardiac muscle and vascular smooth muscle are dependent upon the movement of extracellular calcium ions into these cells through specific ion channels. The effects of nicardipine are more selective to vascular smooth muscle than cardiac muscle. In animal models, nicardipine produced relaxation of coronary vascular smooth muscle at drug levels which cause little or no negative inotropic effect.

12.2 Pharmacodynamics

Hemodynamics

CARDENE I.V. produces significant decreases in systemic vascular resistance. In a study of intra-arterially administered CARDENE I.V., the degree of vasodilation and the resultant decrease in blood pressure were more prominent in hypertensive patients than in normotensive volunteers. Administration of CARDENE I.V. to normotensive volunteers at dosages of 0.25 to 3 mg/hr for eight hours produced changes of <5 mmHg in systolic blood pressure and <3 mmHg in diastolic blood pressure.

An increase in heart rate is a normal response to vasodilation and decrease in blood pressure; in some patients these increases in heart rate may be pronounced. In placebo-controlled trials, the mean increases in heart rate were 7 ± 1 bpm in postoperative patients and 8 ± 1 bpm in patients with severe hypertension at the end of the maintenance period.

Hemodynamic studies following intravenous dosing in patients with coronary artery disease and normal or moderately abnormal left ventricular function have shown significant increases in ejection fraction and cardiac output with no significant change, or a small decrease, in left ventricular end-diastolic pressure (LVEDP). There is evidence that CARDENE I.V. increases blood flow. Coronary dilatation induced by CARDENE I.V. improves perfusion and aerobic metabolism in areas with chronic ischemia, resulting in reduced lactate production and augmented oxygen consumption. In patients with coronary artery disease, CARDENE I.V., administered after beta-blockade, significantly improved systolic and diastolic left ventricular function.

In congestive heart failure patients with impaired left ventricular function, CARDENE I.V. increased cardiac output both at rest and during exercise. Decreases in left ventricular end-diastolic pressure were also observed. However, in some patients with severe left ventricular dysfunction, it may have a negative inotropic effect and could lead to worsened failure.

“Coronary steal” has not been observed during treatment with CARDENE I.V. (Coronary steal is the detrimental redistribution of coronary blood flow in patients with coronary artery disease from underperfused areas toward better perfused areas.) CARDENE I.V. has been shown to improve systolic shortening in both normal and hypokinetic segments of myocardial muscle. Radionuclide angiography has confirmed that wall motion remained improved during increased oxygen demand. (Occasional patients have developed increased angina upon receiving oral nicardipine. Whether this represents coronary steal in these patients, or is the result of increased heart rate and decreased diastolic pressure, is not clear.)

In patients with coronary artery disease, CARDENE I.V. improves left ventricular diastolic distensibility during the early filling phase, probably due to a faster rate of myocardial relaxation in previously underperfused areas. There is little or no effect on normal myocardium, suggesting the improvement is mainly by indirect mechanisms such as afterload reduction and reduced ischemia. CARDENE I.V. has no negative effect on myocardial relaxation at therapeutic doses. The clinical benefits of these properties have not yet been demonstrated.

Electrophysiologic Effects

In general, no detrimental effects on the cardiac conduction system have been seen with CARDENE I.V. During acute electrophysiologic studies, it increased heart rate and prolonged the corrected QT interval to a minor degree. It did not affect sinus node recovery or SA conduction times. The PA, AH, and HV intervals* or the functional and effective refractory periods of the atrium were not prolonged. The relative and effective refractory periods of the His-Purkinje system were slightly shortened.

*PA = conduction time from high to low right atrium; AH = conduction time from low right atrium to His bundle deflection, or AV nodal conduction time; HV = conduction time through the His bundle and the bundle branch-Purkinje system.

Hepatic Function

Because the liver extensively metabolizes nicardipine, plasma concentrations are influenced by changes in hepatic function. In a clinical study with oral nicardipine in patients with severe liver disease, plasma concentrations were elevated and the half-life was prolonged [see Warnings and Precautions (5.3)]. Similar results were obtained in patients with hepatic disease when CARDENE I.V. (nicardipine hydrochloride) was administered for 24 hours at 0.6 mg/hr.

Renal Function

When CARDENE I.V. was given to mild to moderate hypertensive patients with moderate degrees of renal impairment, significant reduction in glomerular filtration rate (GFR) and effective renal plasma flow (RPF) was observed. No significant differences in liver blood flow were observed in these patients. A significantly lower systemic clearance and higher area under the curve (AUC) were observed. When oral nicardipine (20 mg or 30 mg TID) was given to hypertensive patients with impaired renal function, mean plasma concentrations, AUC, and Cmax were approximately two-fold higher than in healthy controls. There is a transient increase in electrolyte excretion, including sodium [see Warnings and Precautions (5.4)].

Acute bolus administration of CARDENE I.V. (2.5 mg) in healthy volunteers decreased mean arterial pressure and renal vascular resistance; glomerular filtration rate (GFR), renal plasma flow (RPF), and the filtration fraction were unchanged. In healthy patients undergoing abdominal surgery, CARDENE I.V. (10 mg over 20 minutes) increased GFR with no change in RPF when compared with placebo. In hypertensive type II diabetic patients with nephropathy, oral nicardipine (20 mg TID) did not change RPF and GFR, but reduced renal vascular resistance.

Pulmonary Function

In two well-controlled studies of patients with obstructive airway disease treated with oral nicardipine, no evidence of increased bronchospasm was seen. In one of the studies, oral nicardipine improved forced expiratory volume 1 second (FEV1) and forced vital capacity (FVC) in comparison with metoprolol. Adverse experiences reported in a limited number of patients with asthma, reactive airway disease, or obstructive airway disease are similar to all patients treated with oral nicardipine.

12.3 Pharmacokinetics

Distribution

Rapid dose-related increases in nicardipine plasma concentrations are seen during the first two hours after the start of an infusion of CARDENE I.V. Plasma concentrations increase at a much slower rate after the first few hours, and approach steady state at 24 to 48 hours. The steady-state pharmacokinetics of nicardipine are similar in elderly hypertensive patients (>65 years) and young healthy adults. On termination of the infusion, nicardipine concentrations decrease rapidly, with at least a 50% decrease during the first two hours post-infusion. The effects of nicardipine on blood pressure significantly correlate with plasma concentrations. Nicardipine is highly protein bound (>95%) in human plasma over a wide concentration range. Following infusion, nicardipine plasma concentrations decline tri-exponentially, with a rapid early distribution phase (α-half-life of 2.7 minutes), an intermediate phase (β-half-life of 44.8 minutes), and a slow terminal phase (γ-half-life of 14.4 hours) that can only be detected after long-term infusions. Total plasma clearance (Cl) is 0.4 L/hr•kg, and the apparent volume of distribution (Vd) using a non-compartment model is 8.3 L/kg. The pharmacokinetics of CARDENE I.V. are linear over the dosage range of 0.5 to 40 mg/hr.

Metabolism and Excretion

CARDENE I.V. has been shown to be rapidly and extensively metabolized by the hepatic cytochrome P450 enzymes, CYP2C8, 2D6, and 3A4. Nicardipine does not induce or inhibit its own metabolism, however, nicardipine has been shown to inhibit certain cytochrome P450 enzymes (including CYP3A4, CYP2D6, CYP2C8, and CYP2C19). Inhibition of these enzymes may result in increased plasma levels of certain drugs, including cyclosporine and tacrolimus (7.3, 7.4). The altered pharmacokinetics may necessitate dosage adjustment of the affected drug or discontinuation of treatment.

After coadministration of a radioactive intravenous dose of CARDENE I.V. with an oral 30 mg dose given every 8 hours, 49% of the radioactivity was recovered in the urine and 43% in the feces within 96 hours. None of the dose was recovered as unchanged nicardipine.

13 NONCLINICAL TOXICOLOGY

13.1 Carcinogenesis, Mutagenesis, Impairment of Fertility

Rats treated with nicardipine in the diet (at concentrations calculated to provide daily dosage levels of 5, 15, or 45 mg/kg/day) for two years showed a dose-dependent increase in thyroid hyperplasia and neoplasia (follicular adenoma/carcinoma). One- and three-month studies in the rat have suggested that these results are linked to a nicardipine-induced reduction in plasma thyroxine (T4) levels with a consequent increase in plasma levels of thyroid stimulating hormone (TSH). Chronic elevation of TSH is known to cause hyperstimulation of the thyroid.

In rats on an iodine deficient diet, nicardipine administration for one month was associated with thyroid hyperplasia that was prevented by T4 supplementation. Mice treated with nicardipine in the diet (at concentrations calculated to provide daily dosage levels of up to 100 mg/kg/day) for up to 18 months showed no evidence of neoplasia of any tissue and no evidence of thyroid changes.

There was no evidence of thyroid pathology in dogs treated with up to 25 mg nicardipine/kg/day for one year and no evidence of effects of nicardipine on thyroid function (plasma T4 and TSH) in man.

There was no evidence of a mutagenic potential of nicardipine in a battery of genotoxicity tests conducted on microbial indicator organisms, in micronucleus tests in mice and hamsters, or in a sister chromatid exchange study in hamsters.

No impairment of fertility was seen in male or female rats administered nicardipine at oral doses as high as 100 mg/kg/day (human equivalent dose about 16 mg/kg/day, 8 times the maximum recommended oral dose).

13.3 Reproductive and Developmental Toxicology

Embryotoxicity, but no teratogenicity, was seen at intravenous doses of 10 mg nicardipine/kg/day in rats and 1 mg/kg/day in rabbits. These doses in the rat and rabbit are equivalent to human IV doses of about 1.6 mg/kg/day and 0.32 mg/kg/day respectively. (The total daily human dose delivered by a continuous IV infusion ranges from 1.2 to 6 mg/kg/day, depending on duration at different infusion rates ranging from 3 to 15 mg/hr as individual patients are titrated for optimal results.) Nicardipine was also embryotoxic when administered orally to pregnant Japanese White rabbits, during organogenesis, at 150 mg/kg/day (a dose associated with marked body weight gain suppression in the treated doe), but not at 50 mg/kg/day (human equivalent dose about 16 mg/kg/day or about 8 times the maximum recommended human oral dose). No adverse effects on the fetus were observed when New Zealand albino rabbits were treated orally, during organogenesis, with up to 100 mg nicardipine/kg/day (a dose associated with significant mortality in the treated doe). In pregnant rats administered nicardipine orally at doses of up to 100 mg/kg/day (human equivalent dose about 16 mg/kg/day) there was no evidence of embryotoxicity or teratogenicity. However, dystocia, reduced birth weight, reduced neonatal survival and reduced neonatal weight gain were noted.

14 CLINICAL STUDIES

Effects In Hypertension

In patients with mild to moderate chronic stable essential hypertension, CARDENE I.V. (0.5 to 4 mg/hr) produced dose-dependent decreases in blood pressure. At the end of a 48-hour infusion at 4 mg/hr, the decreases were 26 mmHg (17%) in systolic blood pressure and 20.7 mmHg (20%) in diastolic blood pressure. In other settings (e.g., patients with severe or postoperative hypertension), CARDENE I.V. (5 to 15 mg/hr) produced dose-dependent decreases in blood pressure. Higher infusion rates produced therapeutic responses more rapidly. The mean time to therapeutic response for severe hypertension, defined as diastolic blood pressure ≤95 mmHg or ≥25 mmHg decrease and systolic blood pressure ≤160 mmHg, was 77 ± 5.2 minutes. The average maintenance dose was 8 mg/hr. The mean time to therapeutic response for postoperative hypertension, defined as ≥15% reduction in diastolic or systolic blood pressure, was 11.5 ± 0.8 minutes. The average maintenance dose was 3 mg/hr.

16 HOW SUPPLIED/STORAGE AND HANDLING

16.1 How Supplied

CARDENE I.V. (nicardipine hydrochloride) injection is clear, pale yellow to yellow color solution supplied as 25 mg/10 mL (2.5 mg/mL) single-dose vial for intravenous infusion after dilution, is available as below:

Strength | NDC Number | Package Size
25 mg/10 mL (2.5 mg/mL) | NDC 43066-029-01 | 10 mL Single-Dose Vial
25 mg/10 mL (2.5 mg/mL) | NDC 43066-029-10 | 10 Single-Dose Vials in carton

16.2 Storage and Handling

Store at controlled room temperature 20° C to 25° C (68° F to 77° F), refer to USP Controlled Room Temperature.

Protect from light, store vials in carton until ready to use.

Discard unused portion.

Manufactured for:

Baxter Healthcare Corporation
Deerfield, IL 60015 USA

Manufacture by:

Maiva Pharma Private Limited
No 32, SIPCOT Industrial Complex,
Phase I, Hosur, Tamil Nadu 635126, India

To report suspected adverse reactions, contact Baxter Healthcare at 1-866-888-2472.

Baxter is a registered trademark of Baxter International Inc.

Cardene is a registered trademark of Chiesi USA, Inc. and is used under license.

U.S. Patent Numbers 7612102 and 7659291

07-19-01-0650

PACKAGE/LABEL PRINCIPAL DISPLAY PANEL

Container Label

NDC 43066-029-01
Rx Only
CARDENE I.V.
(niCARdipine hydrochloride injection)
25 mg/10 mL (2.5 mg/mL)

WARNING: MUST BE DILUTED BEFORE
INFUSION
For intravenous infusion after diluation.
Discard unused portion.
10 mL Single-Dose Vial

*BAR CODE
(01)00343066029012

Store at controlled room temperature 20º to 25º C
(68º to 77º F), refer to USP Controlled Room Temperature.
Protect from light. Store vials in carton until ready to use.
Made in India
Manufactured for:
Baxter Healthcare Corporation
Deerfield, IL 60015 USA
US/225/LB/150 V01
PLC560

Code No.: TN/DRUGS/616/1996
07-02-00-0370

AIN03290

LOT:
EXP:
Varnish free area for lot and
Exp to be printed
18x10mm

Carton Label

NDC 43066-029-10
Rx Only
CARDENE I.V.
(niCARdipine hydrochloride injection)
25 mg/10 mL
(2.5 mg/mL)

WARNING: MUST BE DILUTED BEFORE INFUSION.
For intravenous infusion after dilution.
Discard unused portion
10 x 10 mL Single-Dose Vials

07-01-00-1874

Baxter Logo
Manufactured for:
Baxter Healthcare Corporation
Deerfield, IL 60015 USA

Manufactured by:
Maiva Pharma Private Limited
No 32, SIPCOT Industrial Complex, Phase I,
Honsur, Tamil Nadu 635126, India
AIN03290

Code: TN/DRUGS/616/1996

*BAR CODE
(01)20343066029108

Each mL contains 2.5 mg nicardipine hydrochloride, 1 mg ascorbic acid, 0.525 mg citric acid
monohydrate, 0.09 mg sodium hydroxide and 48 mg sorbitol (neosorb PF) Citric acid monohydrate
and/or sodium hydroxide may have been added to adjust pH to 3.0 to 4.2.

Recommended Dosage: See Prescribing Information.

Store at controlled room temperature 20º to 25º C (68º to 77º F), refer to USP Controlled Room
Temperature.

Protect from light. Store vials in carton until ready to use.

The diluted solution is stable for 24 hours at room temperature.

Cardene is a registered trademark of Chiesi USA, Inc. and is used under license.

US/225/CA/159 V01
PCT410

OVERCODING AREA
Following details also shall be overprinted along
with batch details.

FPO

GTIN XXXXXXXXXXXXXX
S/N XXXXXXXXXX
EXP YYYY/MM
LOT XXXXXXX

NO VARNISH ZONE
50 x 52 mm